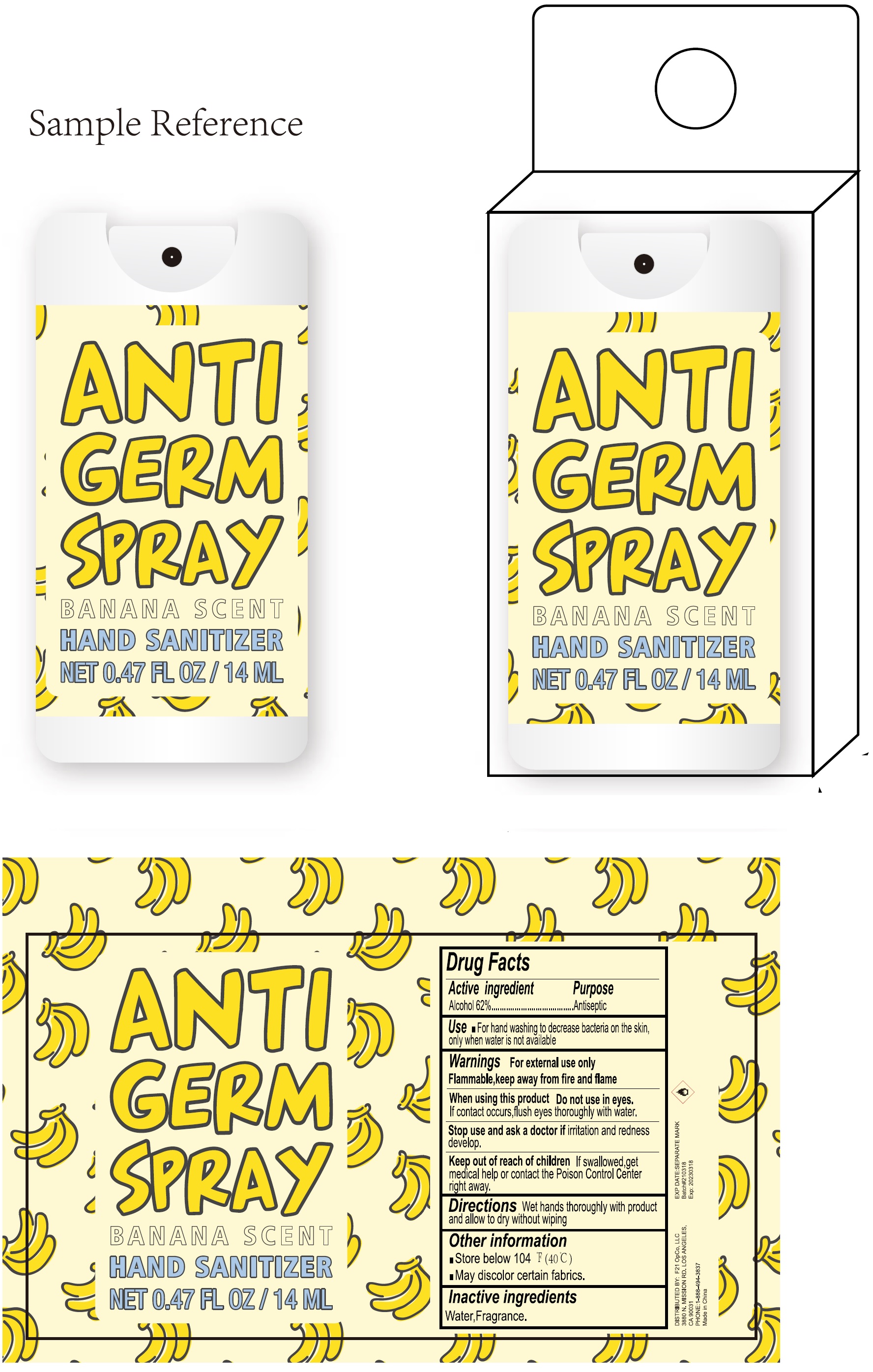 DRUG LABEL: BANANA SCENT ANTI GERM
NDC: 81670-000 | Form: SPRAY
Manufacturer: F21 OpCo, LLC
Category: otc | Type: HUMAN OTC DRUG LABEL
Date: 20231026

ACTIVE INGREDIENTS: ALCOHOL 62 mL/100 mL
INACTIVE INGREDIENTS: WATER

BANANA SCENT ANTI GERM SPRAY

Active ingredient

Alcohol 62%

Purpose

Antiseptic

Use

- For hand washing to decrease bacteria on the skin, only when water are not available

Warnings

For external use only Flammable, keep away from fire and flame

Do not use

If contact occurs, flush eyes thoroughly with water. in eyes.

Stop use and ask a doctor if

irritation or redness develop.

Keep out of the reach of children

If swallowed, get medical help or contact the Poison Control Center right away.

Directions

Wet hands thoroughly with product and allow to dry without wiping

Other Information:

- Store below 104 ºF (40 ºC)
- May discolor certain fabrics.

Inactive ingredients

Water, Fragrance.